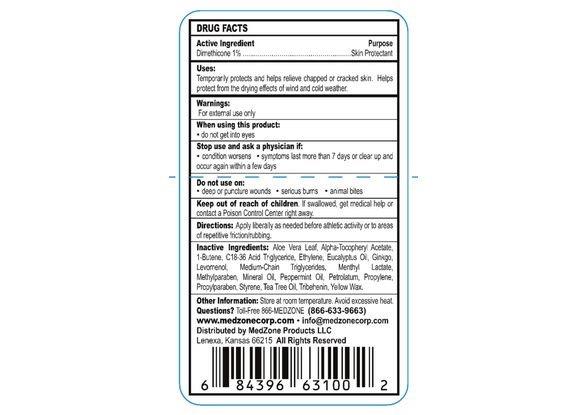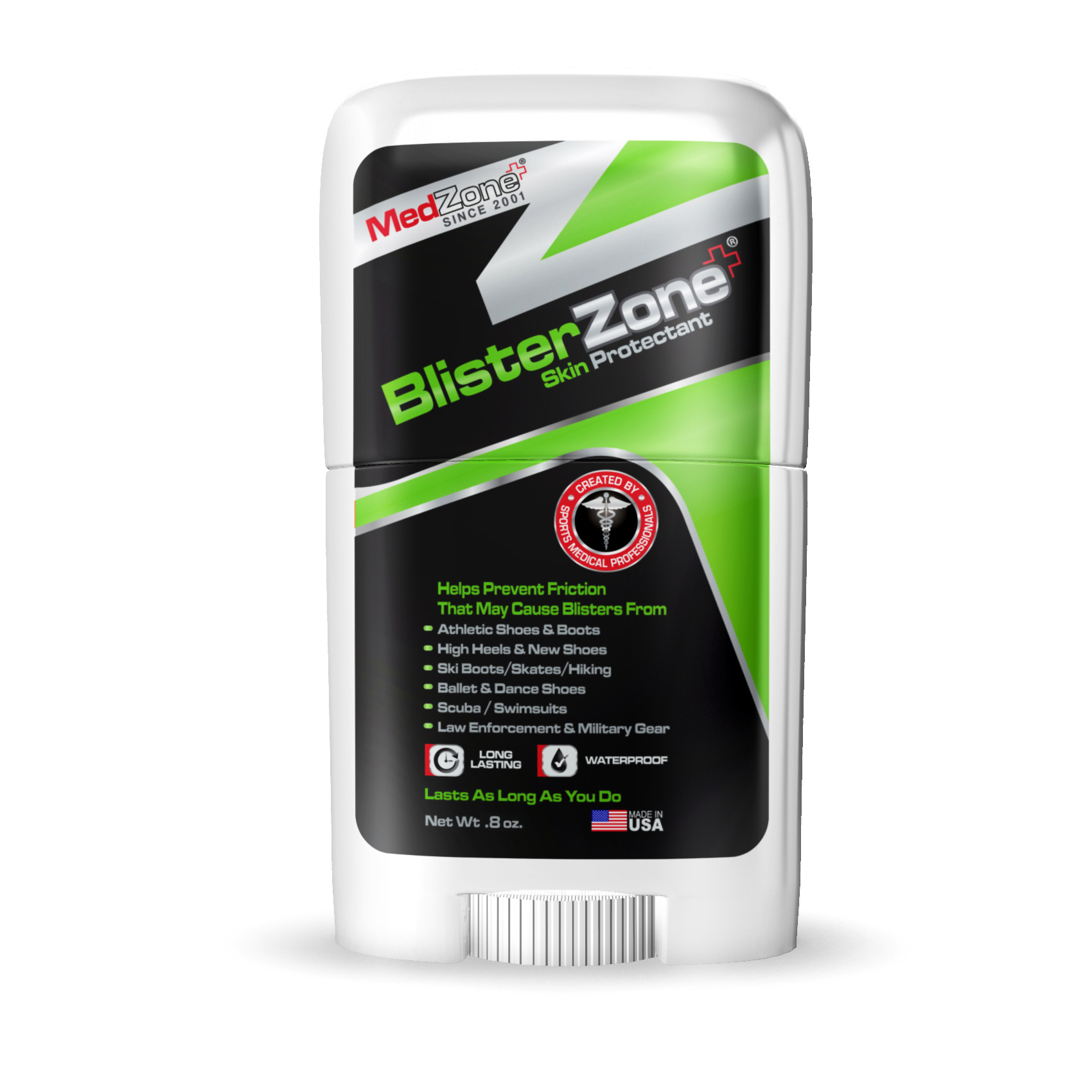 DRUG LABEL: BlisterZone
NDC: 70338-611 | Form: STICK
Manufacturer: MedZone Products LLC
Category: otc | Type: HUMAN OTC DRUG LABEL
Date: 20180212

ACTIVE INGREDIENTS: DIMETHICONE 10 mg/1 g
INACTIVE INGREDIENTS: ALPHA-TOCOPHEROL ACETATE; PEPPERMINT OIL; STYRENE; TRIBEHENIN; ALOE VERA LEAF; YELLOW WAX; 1-BUTENE; ETHYLENE; C18-36 ACID TRIGLYCERIDE; EUCALYPTUS OIL; GINKGO; LEVOMENOL; MEDIUM-CHAIN TRIGLYCERIDES; MENTHYL LACTATE, (-)-; METHYLPARABEN; MINERAL OIL; PETROLATUM; PROPYLENE; PROPYLPARABEN; TEA TREE OIL

Active Ingredient

Dimethicone 1%

Purpose

Skin Protectant

Uses

Temporarily protects and helps relieve chapped or cracked skin. Helps protect from the druing effects of wind and cold weather,

Warnings

For external use only.

When using this product

- do not get into eyes.

Stop use and ask a physician if

- condition worsens
- symptoms last more than 7 days or clear up and occur again within a few days

Do not use on:

- deep or puncture wounds
- serious burns
- animal bites

Keep out of reach of chlidren

If swallowed, get medical help or contact a Poison Control Center right away.

Directions

Apply liberally as needed before athletic activity or to areas of repetitive friction/rubbing

Inactive Ingredients

Aloe Vera Leaf, Alpha-Tocopheryl Acetate, 1-Butene, C18-36 Acid Triglyceride, Ethylene, Eucalyptus Oil, Ginkgo, Levomenol, Medium-Chain Triglycerides, Menthyl Lactate, Methylparaben, Mineral oil, Peppermint Oil, Petrolatum, Propylene, Propylparaben, Styrene, Tea Tree Oil, Tribehenin, Yellow Wax

Other Information

Store at room temperature. Avoid excessive heat.

Questions?

Toll-Free 866-MEDZONE (866-633-9663)

www.medzonecorp.com info@medzonecorp.com

HOW SUPPLIED

Distributed by MedZone Products LLC

Lenexa, Kansas 66215

All rights reserved